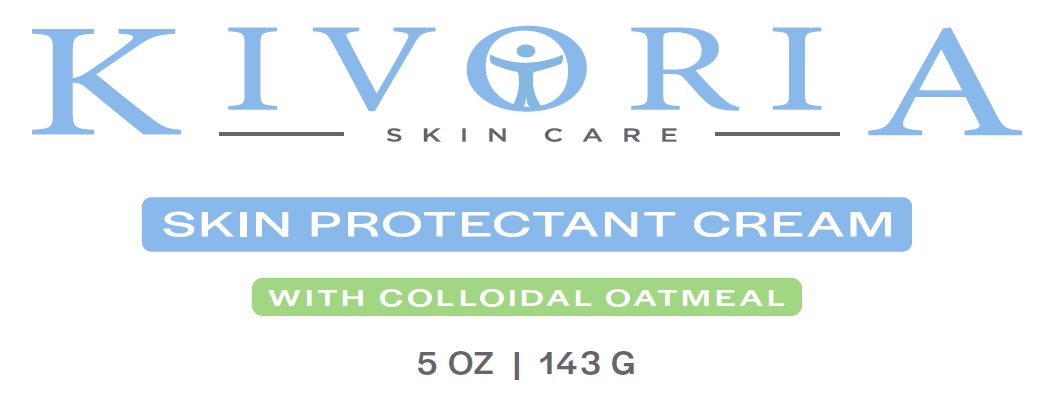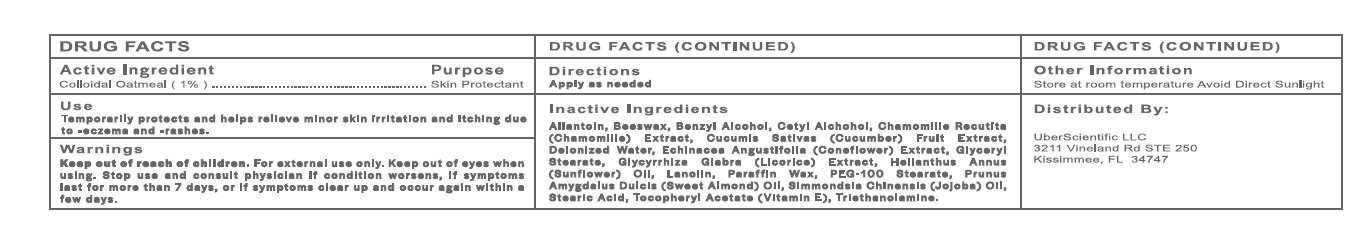 DRUG LABEL: KIVORIA SKIN PROTECTANT
NDC: 71131-200 | Form: CREAM
Manufacturer: UBER SCIENTIFIC
Category: otc | Type: HUMAN OTC DRUG LABEL
Date: 20211228

ACTIVE INGREDIENTS: OATMEAL 1 g/100 g
INACTIVE INGREDIENTS: ALLANTOIN; BENZYL ALCOHOL; CETYL ALCOHOL; ALPHA-TOCOPHEROL; LANOLIN; JOJOBA OIL; GLYCERYL STEARATE/PEG-100 STEARATE; GLYCYRRHIZA GLABRA; WHITE WAX; CHAMOMILE; CUCUMBER FRUIT OIL; WATER; ECHINACEA ANGUSTIFOLIA LEAF; PARAFFIN; STEARIC ACID; TROLAMINE; ALMOND OIL; SUNFLOWER OIL

KIVORIA SKIN PROTECTANT (71131-200)

DRUG FACTS

ACTIVE INGREDIENT

Colloidal Oatmeal

PURPOSE

Skin protectant

USE

Temporarily protects and helps relieve minor skin irritation and itching due to

- eczema and
- rashes

WARNINGS

For external use only. Keep out of eyes when using.

Keep out of reach of children

Stop use and consult physician if condition worsens, if symptoms last for more than 7 days or if symptoms clear up and occur again within a few days.

Directions

Apply as needed.

INACTIVE INGREDIENTS

Allantoln, Beeswax, Banzyl Alcohol, Cetyl Alchohol, Chamomllla Racutlta (Chamomille) Extract, Cucumis S11tiv11s (Cucumber) Fruit Extract, deionized W,iter, Echin,.cee Angustifolie (Coneflower) Extrect, Glyceryl Steerete, Glycyrrhlze Glebre (Licorice) Extrect, Hellenthus Annus (Sunflower) Oil, Lanolin, Paraffin Wax, PEG-100 Stearate, Prunus Amygdelus Oulcis (Sweet Almond) Oil, Simmondsie Chinensis (Jojobe) Oil, Steerlc Acid, Tocopheryl Acet8te (Vltemln E), Trlethenolemlne.

OTHER INFORMATION

Store at room temperature Avoid Direct Sunlight

Distributed By:
UberScientific LLC
3211 Vineland Rd STE 250
Kissimmee, FL 34747

PDP

KIVORIA SKIN CARE

SKIN PROTECTANT CREAM WITH COLLOIDAL OATMEAL

5OZ | 143G